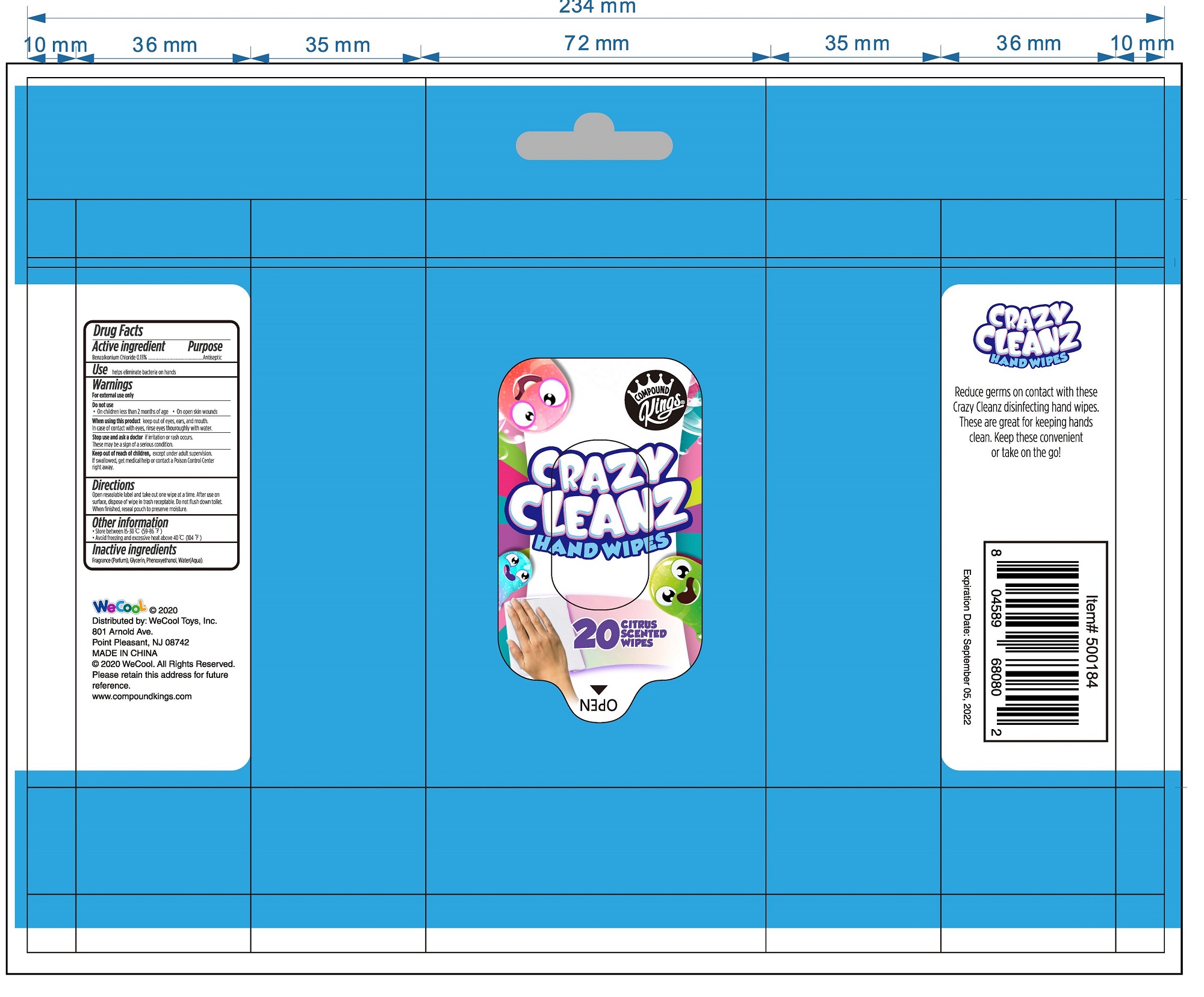 DRUG LABEL: Crazy Cleanz Hand Wipes
NDC: 51706-955 | Form: CLOTH
Manufacturer: Landy International
Category: otc | Type: HUMAN OTC DRUG LABEL
Date: 20220321

ACTIVE INGREDIENTS: BENZALKONIUM CHLORIDE 0.13 g/100 g
INACTIVE INGREDIENTS: PHENOXYETHANOL; GLYCERIN; WATER

51706-955 Crazy Cleanz Hand Wipes 0.13% Benzalkonium chloride

Active Ingredient(s)

Benzalkonium Chloride 0.13%

Purpose

Antiseptic

Use

helps eliminate bacteria on hands

Warnings

For external use only
Do not use
●On children less than 2 months of age
●On open skin wounds
When using this product keep out of eyes, ears, and mouth.
In case of contact with eyes, rinse eyes thouroughly with water.
Stop use and ask a doctor if irritation or rash occurs.
These may be a sign of a serious condition.

Keep out of reach of children, except under adult supervision.
If swallowed, get medical help or contact a Poison Control Center right away.

Directions

Open resealable label and take out one wipe at a time. After use 0n
surface, dispose of wipe in trash receptable. Do not flush down toilet.
When finished, reseal pouch to preserve moisture.

Other information

- Store between 15-30C (59-86F)
- Avoid freezing and excessive heat above 40C (104F)

Inactive ingredients

Fragrance (Parfum), Glycerin, Phenoxyethanol, Water(Aqua).